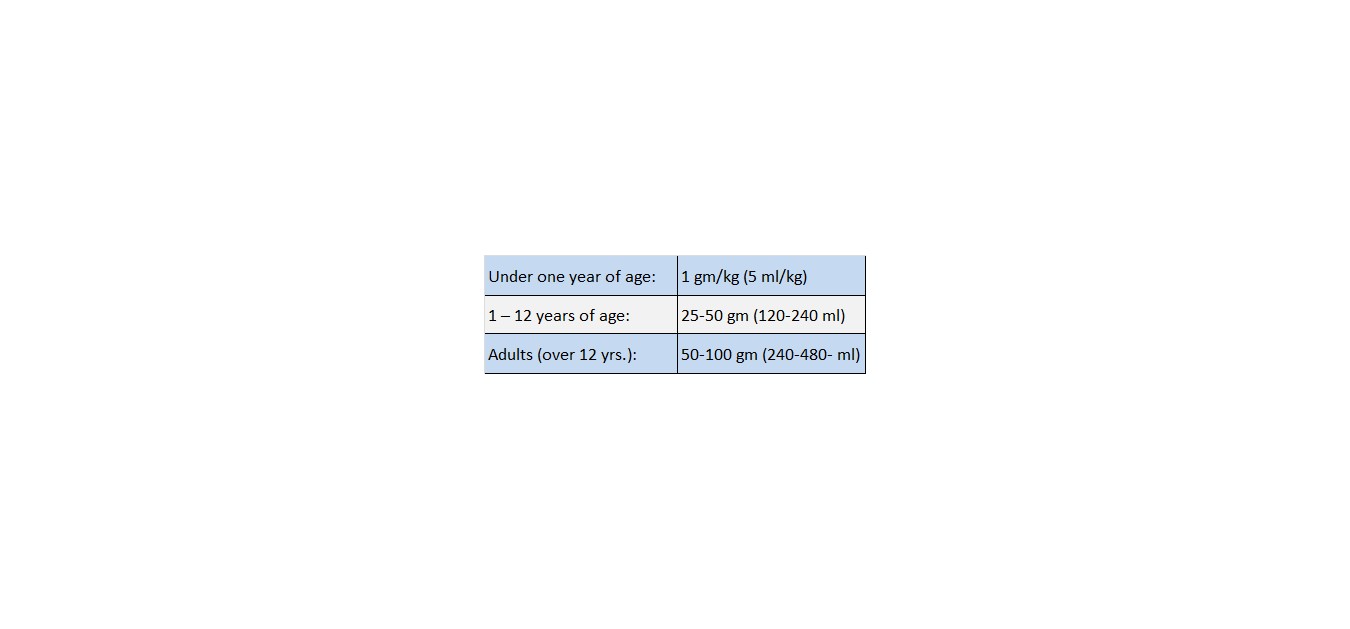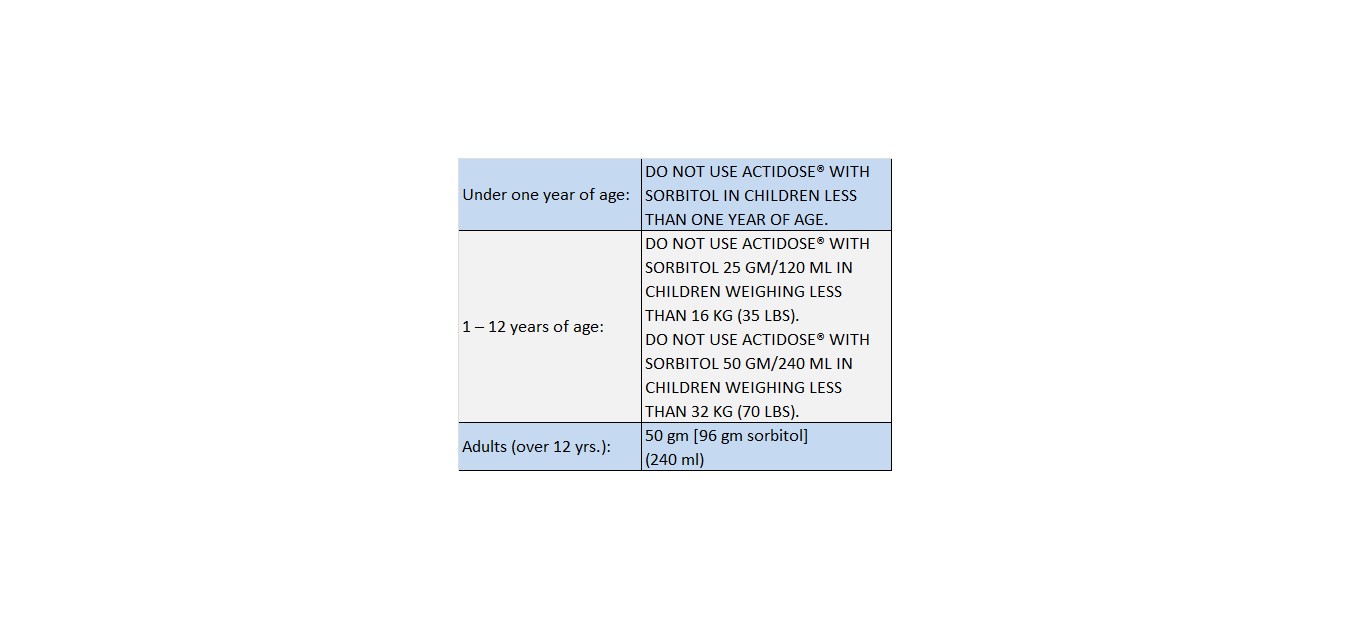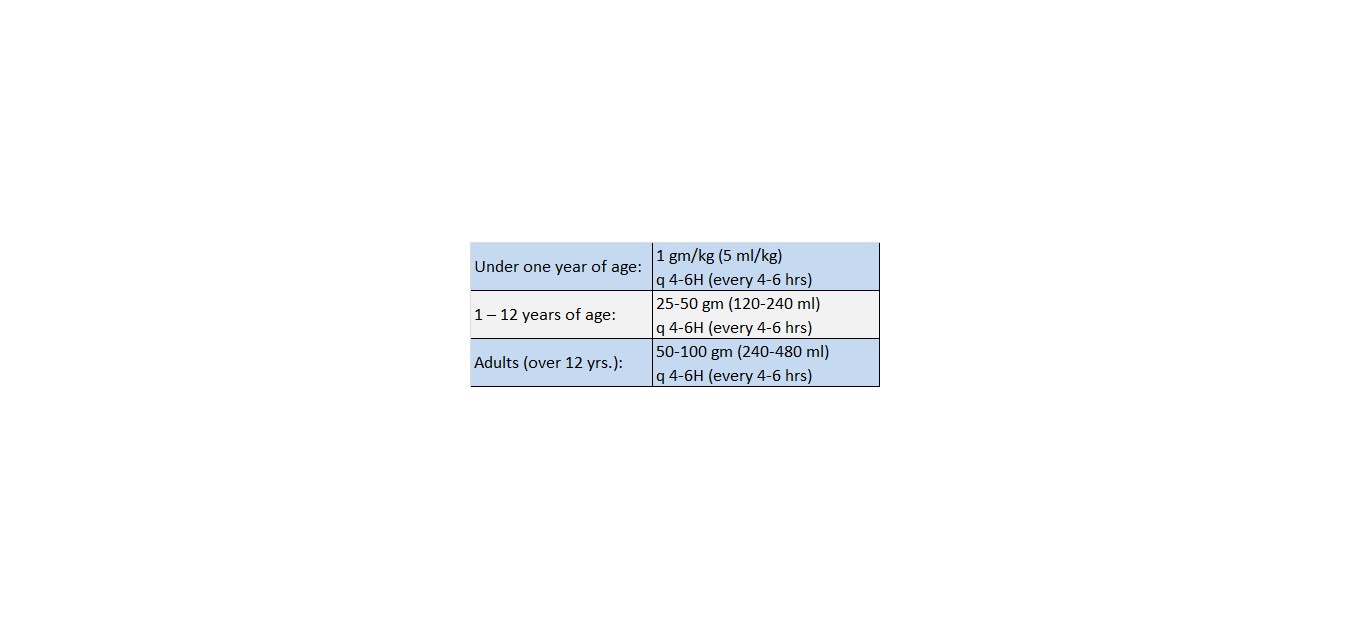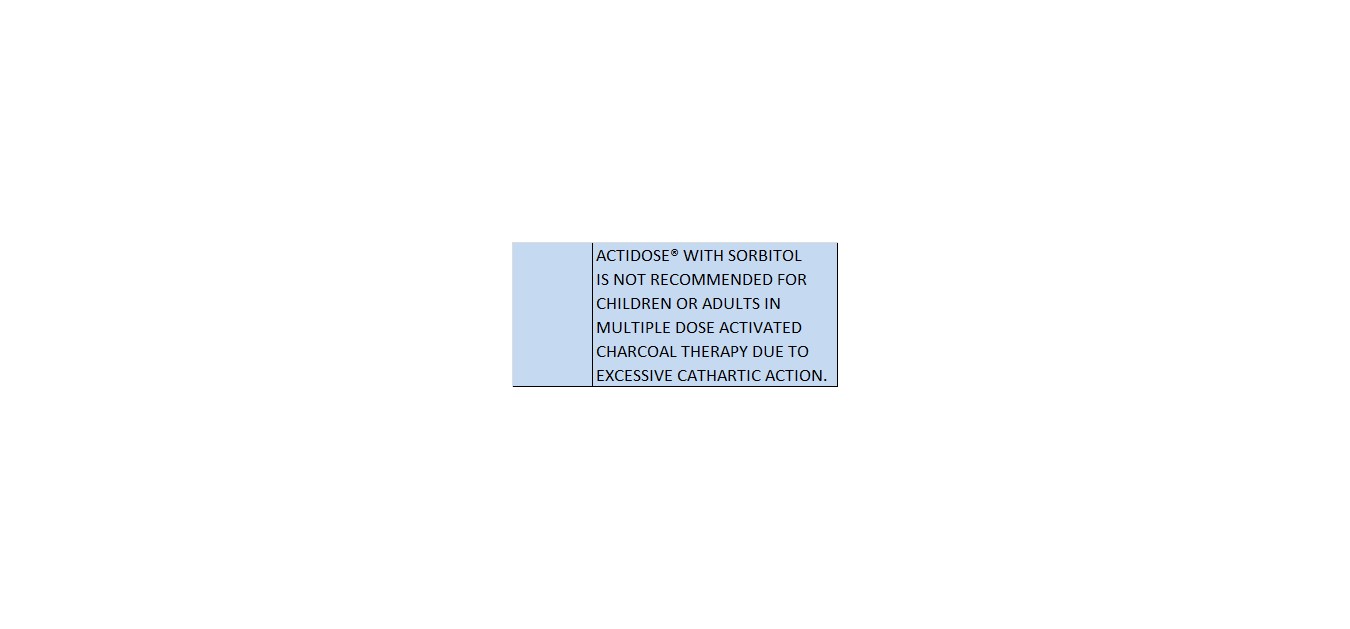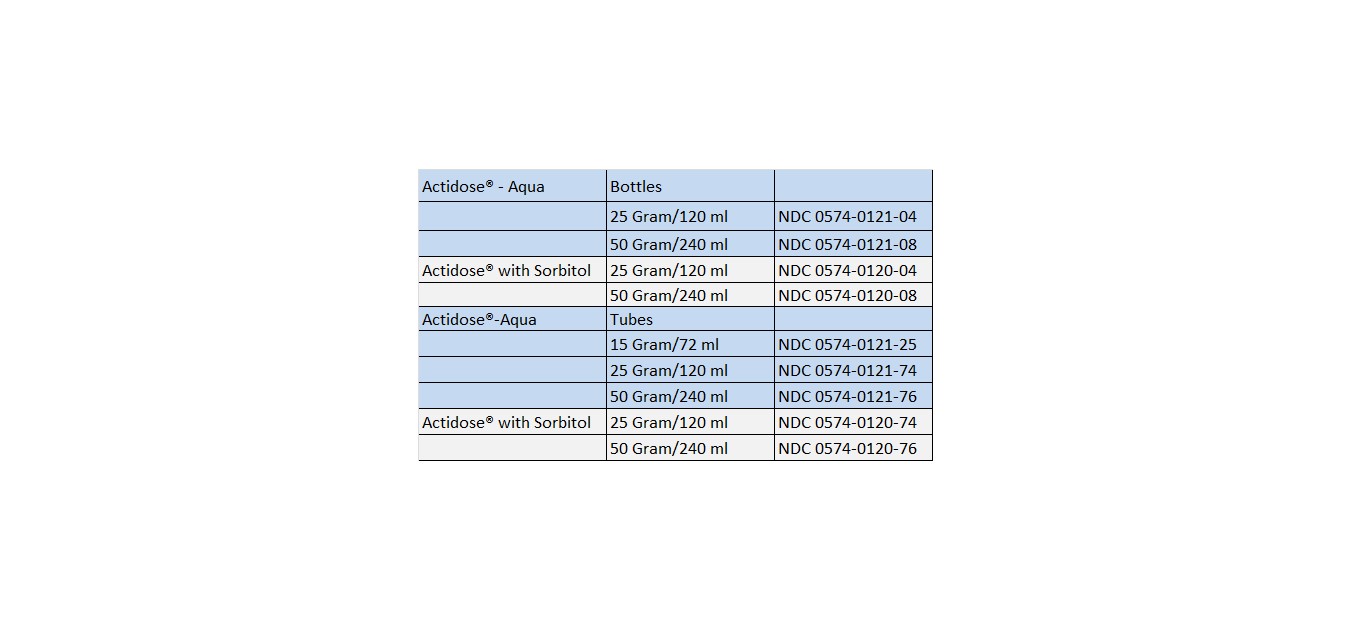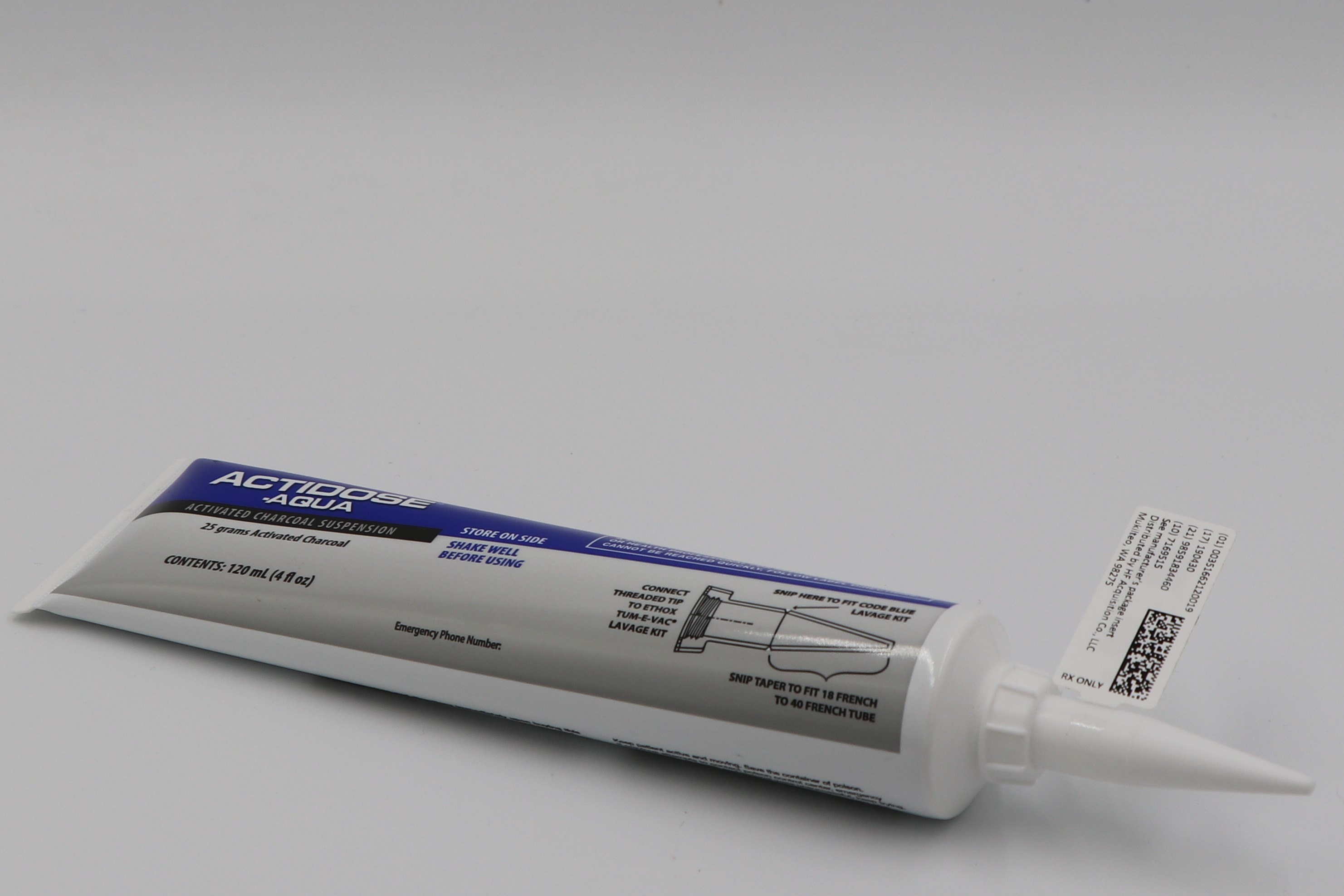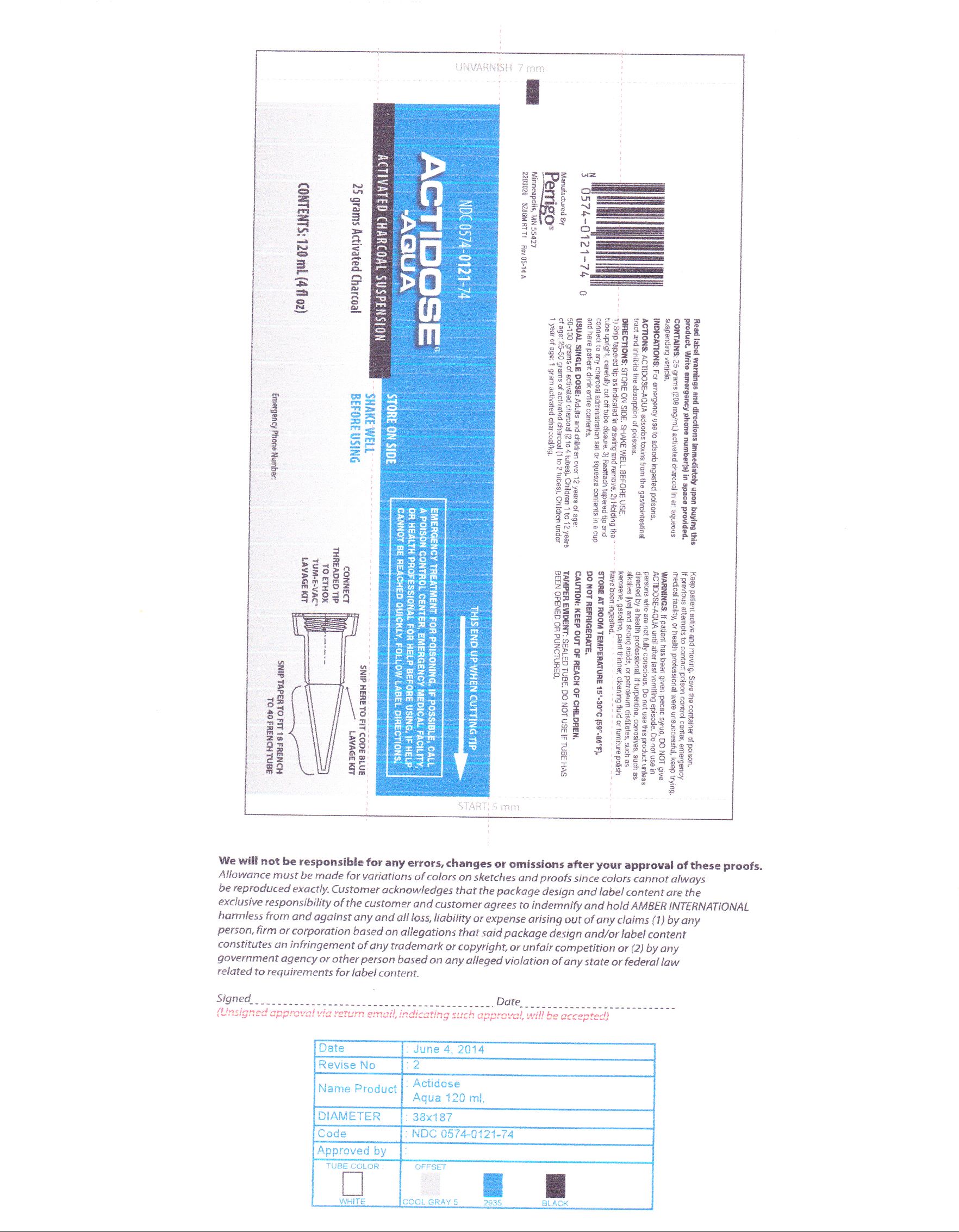 DRUG LABEL: ACTIVATED CHARCOAL
NDC: 51662-1200 | Form: SUSPENSION
Manufacturer: HF Acquisition Co LLC, DBA HealthFirst
Category: prescription | Type: HUMAN PRESCRIPTION DRUG LABEL
Date: 20200219

ACTIVE INGREDIENTS: ACTIVATED CHARCOAL 208 mg/1 mL
INACTIVE INGREDIENTS: WATER; ANHYDROUS CITRIC ACID; SUCROSE; PROPYLENE GLYCOL; GLYCERIN

ACTIDOSE-AQUA 25grams ACTIVATED CHARCOAL TUBE

SPL UNCLASSIFIED

ACTIDOSE® WITH SORBITOL

ACTIDOSE®-AQUA

ACTIVATED CHARCOAL SUSPENSION

DESCRIPTION

Actidose® with Sorbitol: Actidose® with Sorbitol, ready-to-use activated charcoal suspension with sorbitol, contains 25 gm or 50 gm of activated charcoal, and 48 gm or 96 gm of sorbitol, respectively, in an aqueous suspension with a unique preservative system. Each milliliter contains 208 mg (0.208 gm) of activated charcoal and 400 mg (0.400 gm) of sorbitol. Sorbitol reduces the gritty sensation associated with activated charcoal, imparts a sweet taste which enhances patient compliance, and usually produces a cathartic effect.

Actidose®-Aqua: Actidose®-Aqua, ready-to-use activated charcoal suspension, contains 15 gm, 25 gm or 50 gm of activated charcoal in an aqueous suspension with a unique preservative system. Each milliliter contains 208 mg (0.208 gm) of activated charcoal.

WARNINGS

If patient has been given ipecac syrup, DO NOT give ACTIDOSE® WITH SORBITOL or ACTIDOSE®-AQUA until after last vomiting episode. Do not use in persons who are not fully conscious. Do not use this product unless directed by a health professional, if turpentine, corrosives, such as alkalies (lye) and strong acids, or petroleum distillates, such as kerosene, gasoline, paint thinner, cleaning fluid or furniture polish, have been ingested. This product is not recommended for use in children weighing less than 32 kg, or during multiple dose activated charcoal therapy since excessive catharsis and significant fluid and electrolyte abnormalities may occur.

Keep this and all drugs out of the reach of children.

Do not use Actidose® with Sorbitol or Actidose®-Aqua in any person known to have a rare autosomal recessive genetic intolerance to fructose. Do not use Actidose® with Sorbitol in patients who are dehydrated. Actidose® with Sorbitol may cause excessive diarrhea.

CLINICAL PHARMACOLOGY

Activated Charcoal:

Activated charcoal is produced by pyrolysis of organic material, such as wood, and an activation process which cleanses and fragments the charcoal by exposure to an oxidizing gas compound of steam, oxygen, and acids at high temperatures resulting in increased surface area through the creation of numerous external and internal pores. These pores serve as reservoirs to adsorb substances admixed with activated charcoal, making it a useful adsorbent for specified toxins.

Activated charcoal is pharmacologically inert and is not absorbed in the gastrointestinal tract. Activated charcoal will adsorb a variety of organic and inorganic substances, but is especially effective in adsorbing compounds within a molecular weight range of 100 to 1,000 Daltons (AMU’s).1 Several other physiologic and physicochemical factors influence the adsorptive capacity of activated charcoal including: pH, charcoal: drug ratio, gastric contents, and adsorption kinetics.2

Much of the published scientific literature which studied the adsorptive capacity of activated charcoal was conducted using in vitro models. A considerable amount of the research may be invalid since the effects of physiologic pH were not taken into consideration or held constant. Using research models which simulate the gastric environment, some toxins were not adsorbed by activated charcoal. This data was inappropriately extended to imply that activated charcoal did not adsorb a toxin and therefore had no efficacy in the management of that type of poisoning incident. However, the research failed to consider that the increased pH of the small intestine provides a receptive environment for the adsorption of the toxin by activated charcoal. Activated charcoal will effectively adsorb acidic, alkaline and neutral substances (not to suggest use of activated charcoal in poisonings caused by corrosive agents2). The extent of adsorption will be dependent upon the relative solubility of the drug at a specified pH.

The optimal dosage ratio of activated charcoal to toxin is described as 10:1.3,4,17,18 Numerous factors contribute to and interfere with adsorptive capacity, therefore, the 10:1 ratio may not be valid in the clinical setting. Furthermore, a primary application of activated charcoal is in adult patients who have intentionally ingested a toxin for drug abuse or suicidal purposes. These patients may not freely provide information about the substance or amount ingested, or have a decreased level of consciousness. Under these conditions it is difficult to determine the ingestion history, making it impractical to use the 10:1 ratio. The 10:1 ratio is also impractical when large amounts of toxin have been ingested (i.e., an overdose of 50 gm of aspirin would then require 500 gm [1.1 lbs.] of activated charcoal).

Gastric contents may also compete with ingested toxins and compromise the adsorption of the toxins by activated charcoal.2 If activated charcoal is to be administered to a patient known to have ingested a large meal in close proximity to the time of treatment, a larger dose of activated charcoal may be appropriate.

Under appropriate physiologic conditions activated charcoal adsorbs toxins instantaneously. This adsorptive process is reversible and an equilibrium between free and bound toxin will exist. According to the law of mass action the amount of free drug decreases as the dose of activated charcoal increases. Therefore, large doses of activated charcoal can favor the equilibrium toward greater toxin adsorption and efficacy. There is limited evidence that desorption of a toxin from activated charcoal may occur.19 Therefore, there is a potential for toxin readsorption and enhanced toxicity. The current standard of care is to administer a cathartic with single doses of activated charcoal to hasten the elimination of the toxin/activated charcoal complex from the gastrointestinal tract.5 Cathartics should be used with extreme care during multiple dose activated charcoal therapy and it is not recommended to use a cathartic with each dose of activated charcoal.5

Sorbitol:

Sorbitol is a hexahydric sugar alcohol which primarily serves as an osmotic cathartic in Actidose® with Sorbitol.6 A secondary advantage of using sorbitol is as a palatability enhancer to decrease the innate gritty texture of activated charcoal and to provide a sweet vehicle to increase patient compliance. Sorbitol is poorly absorbed during its transit through the gastrointestinal tract. Absorbed sorbitol is metabolized by the liver and slowly converted to fructose. Insulin is not necessary for intracellular transport of sorbitol, therefore customary cathartic doses can be safely used by patients with diabetes mellitus.

As a hyperosmotic cathartic sorbitol produces a hygroscopic action resulting in increased water in the large intestine and increased intraluminal pressure which stimulates catharsis. Studies have been conducted in healthy adult human volunteers using therapeutic amounts of activated charcoal and sorbitol.8,9 Catharsis of activated charcoal occurred in an average of 1.0 - 1.5 hours and persisted for 8 - 12 hours. Fourteen poisoned patients are reported in one series representing a wide range of toxins and dosages of sorbitol resulting in the onset of catharsis in an average of 7.7 hours.10 The onset of action may be expected to be longer in patients who have ingested toxins which decrease bowel motility, such as pharmacological agents and plants with anticholinergic properties, and drugs like narcotics.20

Sorbitol does not compromise the adsorptive capacity of activated charcoal.11, 12

INDICATIONS & USAGE

Actidose® with Sorbitol and Actidose®-Aqua should be used in a supervised medical facility or under the direction of a physician or poison control center.

Actidose® with Sorbitol and Actidose®-Aqua are indicated in the management of many types of poisoning emergencies when a toxin has been ingested or when indicated for a limited number of systemic poisonings resulting from parenteral overdosage or when the toxin has been totally absorbed. If physiologic conditions are optimal, activated charcoal most effectively adsorbs toxins with a molecular weight of 100 - 1,000 Daltons (AMU’s).1 Activated charcoal may not be as effective in adsorbing low molecular weight substances such as aliphatic alcohols (methanol, isopropanol, ethanol, etc.) metals (iron, lead, mercury, etc.) and elements such as lithium.2. Two animal studies have demonstrated that very toxic and low molecular weight cyanide compounds are adsorbed by activated charcoal.21,22 The use of activated charcoal in toxic emergencies involving these substances is not contraindicated. Many poisonings involve multiple substances, therefore, Actidose® with Sorbitol and Actidose®-Aqua may be effective in adsorbing some or all of the ingested toxins.

Adsorption of a toxin by activated charcoal can occur anywhere in the gastrointestinal tract. However, to use Actidose® with Sorbitol or Actidose®-Aqua most effectively it is important to administer it as soon as possible to the victim of an ingested exposure. The longer the delay between the ingestion of the toxin and administration of activated charcoal, the less effective it will be. If syrup of ipecac is being used to produce emesis, administration of Actidose® with Sorbitol or Actidose®-Aqua is customarily delayed until 30 – 60 minutes after conclusion of emesis. In a study which used syrup of ipecac, 60 ml, activated charcoal did not interfere with the emetic effect of syrup of ipecac.23

If gastric lavage is being used to facilitate stomach evacuation a single dose of activated charcoal can be administered in the early stages of gastric lavage. If this technique is utilized, Actidose®-Aqua, which does not contain sorbitol, should be used. Upon completion of gastric lavage Actidose® with Sorbitol can be instilled via the lavage tube. The only disadvantage to the use of activated charcoal in this fashion is that the gastric lavage returns will be black, thus making it difficult to evaluate what the patient ingested by visual examination. The primary advantage of this therapy is that activated charcoal can be administered early to the patient. The convenient packaging of Actidose® with Sorbitol and Actidose®-Aqua (except the 15gm/72ml size) in a squeeze bottle with a tapered nozzle expedites emergency treatment, allowing attachment to a gastric lavage tube and administration of contents.

The most common application of activated charcoal is in acute toxic exposures where Actidose® with Sorbitol and Actidose®-Aqua can adsorb toxins thereby preventing their absorption. Activated charcoal can also be used in some toxic emergencies when absorption is complete or exposure was via a parenteral route. This application usually involves repetitive or multiple doses of activated charcoal.

Multiple doses of activated charcoal may be useful in adsorbing toxins which undergo enterohepatic circulation.13 Drugs which are subject to biliary secretion such as digitoxin are constantly secreted into the gastrointestinal tract and are reabsorbed resulting in prolonged toxicity. Frequent doses of activated charcoal can adsorb those toxins thereby preventing their reabsorption and enhancing toxin elimination through the gastrointestinal tract.

Multiple dose activated charcoal is also used in what is termed gastrointestinal dialysis.14 There are only a limited number of toxins which may be eliminated by this method. Clinical judgement and the toxin’s pharmacokinetic parameters must be considered to determine the applicability of this treatment which is not universally applicable.24 The toxin passively diffuses along a concentration gradient between blood which is perfusing the gastrointestinal tract and the luminal fluids. The multiple doses of activated charcoal adsorb the toxin thereby preventing its reabsorption further maximizing the concentration gradient which permits diffusion of even more toxin into the gastric lumen. Compounds most effectively transferred by this mechanism are lipophilic, uncharged and not excessively bound to proteins. Phenobarbital and theophylline are examples of toxins which can be eliminated more rapidly by this method.15,16

Actidose® with Sorbitol should not be used in each dose of the multiple dose activated charcoal regimen unless it is necessary to produce catharsis. Actidose® with Sorbitol contains sorbitol which may produce excessive catharsis and resultant fluid and electrolyte problems if used at each dosing interval (see Precautions).9,25 Actidose®-Aqua should be used at dosage intervals when Actidose® with Sorbitol is not being used. CATHARTICS SHOULD BE USED CAUTIOUSLY AND ONLY INTERMITTENTLY DURING MULTIPLE DOSE ACTIVATED CHARCOAL THERAPY.

If catharsis of activated charcoal does not occur following the use of Actidose® with Sorbitol within 4 - 8 hours, an additional sorbitol dose of 1.5 gm/kg may be administered. Or, if desired, a saline cathartic such as magnesium citrate may be used if the patient’s renal function is not impaired. Actidose® with Sorbitol and Actidose®-Aqua are formulated in palatable vehicles which eliminate the need to add additional taste or consistency enhancers. The use of supplementary chemicals, syrups, or dairy products should be avoided since their addition may compromise the adsorptive capacity of Actidose® with Sorbitol and Actidose®-Aqua.

CONTRAINDICATIONS

There are no known absolute contraindications to the use of activated charcoal, however, it is not an equally effective adsorbent for all toxins. It should be used with caution, if at all, in patients who have ingested corrosive agents since the activated charcoal may obscure endoscopic visualization of esophageal and gastric lesions produced by the corrosive. The use of a cathartic with activated charcoal may not be advised if a patient has significant fluid or electrolyte abnormalities. Actidose® with Sorbitol should not be used in infants due to the possibility of excessive catharsis. Young children should not receive cathartic doses of sorbitol unless hospitalized and under the immediate care of a physician.

USE IN CHILDREN

Actidose® with Sorbitol is not recommended in children less than one year of age.

USE IN PREGNANCY OR DURING LACTATION

Safe use during pregnancy and lactation has not been established. Actidose® with Sorbitol and Actidose®-Aqua should be used during pregnancy or lactation only if the potential benefit justifies the potential risk. No teratogenic effects have been noted in rabbits or rats.

PRECAUTIONS

Actidose® with Sorbitol and Actidose®-Aqua should be used in a supervised medical facility or under the direction of a physician or poison control center.

Actidose® with Sorbitol and Actidose®-Aqua are adjuncts in the management of poisoning emergencies. Prior to the use of activated charcoal, proper basic life support measures must be implemented as well as the appropriate gastric emptying technique if indicated.

When Actidose® with Sorbitol or Actidose®-Aqua are used to treat a poisoning emergency, the patient and health care providers should be aware that activated charcoal will produce black stools. These stools may be diarrhetic and may persist for several hours.

Actidose® with Sorbitol may produce a profound cathartic effect and proper attention should be given to the patient’s fluid and electrolyte needs. Actidose® with Sorbitol should be used cautiously in patients receiving multiple dose activated charcoal. If Actidose® with Sorbitol is used at each dosage interval, profound catharsis may develop which could result in dehydration, hypotension and significant electrolyte and fluid abnormalities.

A study conducted in healthy adult human volunteers who ingested therapeutic amounts of activated charcoal and sorbitol resulted in severe prolonged diarrhea, but no significant changes were noted in serum electrolytes or osmolality, BUN, or the metabolic profile as compared to the control.8

Gastrointestinal obstruction from activated charcoal may occur as a consequence of toxin-induced antiperistaltic effects. Actidose® with Sorbitol and Actidose®-Aqua should be used cautiously in patients who have been exposed to toxins which interfere with gastrointestinal tract peristalsis (i.e., anticholinergics, opioids, etc.). Bowel sounds should be frequently monitored to assess peristaltic action, especially in patients undergoing multiple dose activated charcoal therapy.

ADVERSE REACTIONS

Activated charcoal with sorbitol has produced severe hypernatremic dehydration when used in excessive amounts in pediatric patients.25, 27

Aspiration of activated charcoal has been reported to produce airway obstruction and a limited number of fatalities have occurred. 28,29,30,31 Bronchiolitis obliterans resulting in death has developed several weeks after the aspiration of activated charcoal.32

Gastrointestinal obstruction associated with the use of multiple dose activated charcoal therapy has been reported.33 An overdose of carbamazepine was responsible for the antiperistaltic effects which led to bowel obstruction.

DOSAGE & ADMINISTRATION

Prior to administration of Actidose® with Sorbitol or Actidose®-Aqua, shake the container thoroughly for a minimum of 30 seconds. After administration of either Actidose® with Sorbitol or Actidose®-Aqua, the container should be thoroughly rinsed with water and any residue should be administered to the patient to ensure that the entire dose has been delivered.

Single Dose - Actidose®-Aqua

Single Dose - Actidose® with Sorbitol

Multiple Dose - Actidose®-Aqua

Multiple Dose - Actidose® with Sorbitol

HOW SUPPLIED

ACTIDOSE-AQUA is supplied in the following dosage forms.
NDC 51662-1200-1

25grams ACTIVATED CHARCOAL TUBE

HF Acquisition Co LLC, DBA HealthFirst
Mukilteo, WA 98275

Also supplied in the following manufactures dosage forms

REFERENCES

1.
Activated Charcoal, Antidotal and Other Medicinal Uses, Marcel Dekker, New York, 1980.
2.
Clinical Pharmacokinetics. 1982; 7: 465-489.
3.
Handbook of Common Poisonings in Children, American Academy of Pediatrics, Evanston, 1983.
4.
Am J Emerg Med. 1985; 3: 280-283.
5.
Poisindex Information System, Micromedix, Denver, 1991.
6.
J Pediatrics. 1981; 98: 157-158.
7.
Diabetes Care. 1978; 1: 223-230.
8.
Clinical Toxicology. 1985; 22: 529-536.
9.
Ann. Emerg . Med. 1985; 14: 1152-1155.
10.
Clinical Toxicology. 1985; 23: 579-587.
11.
J. Pharmacol . Exp. Ther . 1982; 221: 656-663.
12.
Am. J. Hosp. Pharm. 1978, 35: 1355-1359.
13.
Lancet. 1981; 2: 1177-1178.
14.
NEJM. 1982; 307: 676-678.
15.
NEJM. 1982; 307: 642-644.
16.
Clin . Pharmacol . Therap. 1983; 34: 663-666.
17.
Medical Toxicology. New York, Elsevier, 1988.
18.
Clinical Management of Poisoning and Drug Overdose. Philadelphia, W.B. Saunders Co., 1990.
19.
Arch Intern Med. 1987; 147: 1390-1392.
20.
Clin Toxicol . 1989; 27: 91-99.
21.
Ann Emerg Med. 1988; 17: 595-598.
22.
Ann Emerg Med. 1990; 19: 453.
23.
Ann Emerg Med. 1987; 16: 164-166.
24.
Ann Emerg Med. 1991; 20: 529-531.
25.
J. Pediatrics. 1986; 109: 719-722.
26.
Ann Emerg Med. 1986; 15: 1214-1218.
27.
J. Pediatrics. 1988; 112: 333.
28.
Vet Hum Toxicol . 1989; 31: 335.
29.
B Med J. 1988; 297: 459-460.
30.
NCMJ. 1990; 51: 79-80.
31.
Ann Emerg Med. 1981; 10: 528-529.
32.
Chest. 1989; 96: 672-674.
33.
J Emerg Med. 1986; 4: 401-407.

SPL UNCLASSIFIED

Manufactured By

Perrigo®

Minneapolis, MN 55427

2122016

(04-12)